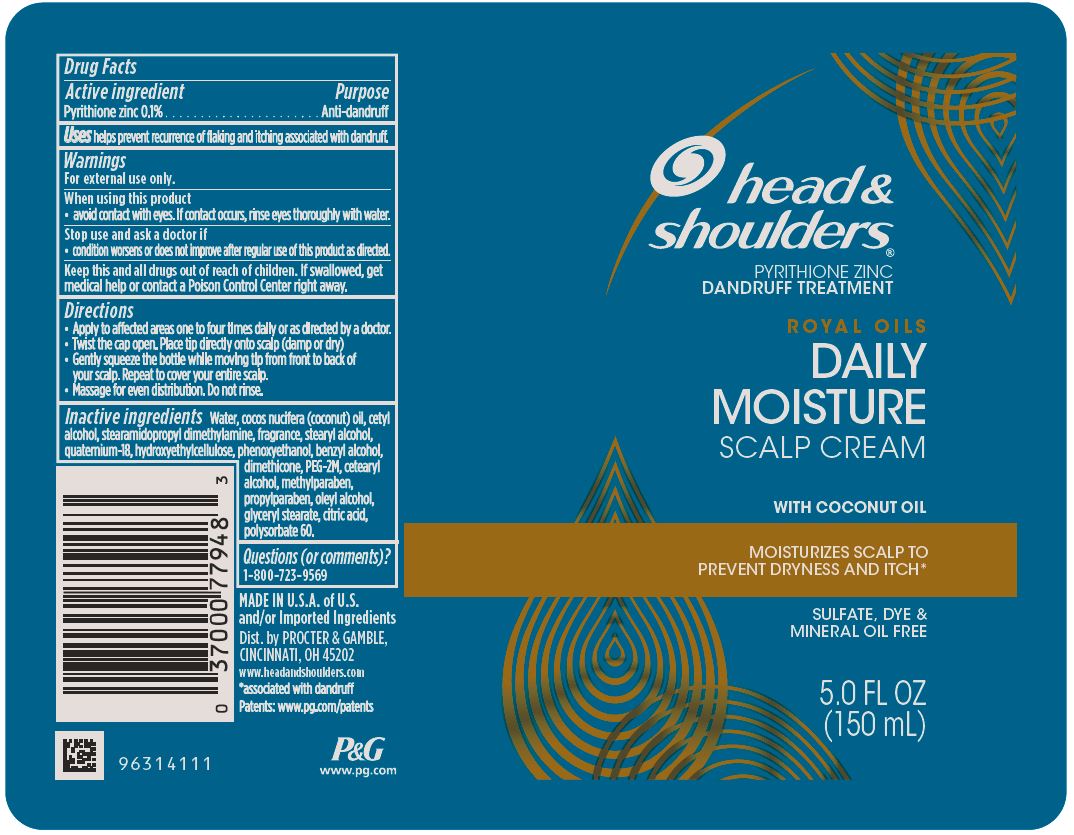 DRUG LABEL: Head and Shoulders Royal Oils Daily Moisture Scalp
NDC: 69423-307 | Form: CREAM
Manufacturer: The Procter & Gamble Manufacturing Company
Category: otc | Type: HUMAN OTC DRUG LABEL
Date: 20251218

ACTIVE INGREDIENTS: PYRITHIONE ZINC 0.1 g/100 mL
INACTIVE INGREDIENTS: CETOSTEARYL ALCOHOL; POLYSORBATE 60; DIMETHICONE; OLEYL ALCOHOL; POLYETHYLENE OXIDE 100000; WATER; STEARYL ALCOHOL; CETYL ALCOHOL; PHENOXYETHANOL; BENZYL ALCOHOL; CITRIC ACID MONOHYDRATE; STEARAMIDOPROPYL DIMETHYLAMINE; QUATERNIUM-18; COCONUT OIL; GLYCOL STEARATE; METHYLPARABEN; PROPYLPARABEN

Head and Shoulders® Royal Oils Daily Moisture Scalp Cream

Drug Facts

Active ingredient

Pyrithione zinc 0.1%

Purpose

Anti-dandruff

Uses

helps prevent recurrence of flaking and itching associated with dandruff.

Warnings

For external use only.

When using this product

- avoid contact with eyes. If contact occurs, rinse eyes thoroughly with water.

Stop use and ask a doctor if

- condition worsens or does not improve after regular use of this product as directed.

KEEP OUT OF REACH OF CHILDREN

Keep this and all drugs out of reach of children. If swallowed, get medical help or contact a Poison Control Center right away.

Directions

• Apply to affected areas one to four times daily or as directed by a doctor.

• Twist the cap open. Place tip directly onto scalp (damp or dry)

• Gently squeeze the bottle while moving tip fromfront to back of your scalp. Repeat to cover your entire scalp.

• Massage for even distribution. Do not rinse.

Inactive ingredients

Water, cocos nucifera (coconut) oil, cetyl alcohol, stearamidopropyl dimethylamine, fragrance, stearyl alcohol, quaternium-18, hydroxyethylcellulose, phenoxyethanol, benzyl alcohol, dimethicone, PEG-2M, cetearyl alcohol, methylparaben, propylparaben, oleyl alcohol, glyceryl stearate, citric acid, polysorbate 60.

Questions (or comments)?

1-800-723-9569

Dist. by PROCTER & GAMBLE,
CINCINNATI, OH 45202

PRINCIPAL DISPLAY PANEL - 150 mL Bottle Label

head &
shoulders®
pyrithione zinc dandruff treatment

ROYAL OILS

DAILY MOISTURE

SCALP CREAM

WITH COCONUT OIL

MOISTURIZES SCALP TO

PREVENT DRYNESS AND ITCH*

SULFATE, DYE &

MINERAL OIL FREE

5.0 FL OZ
(150 mL)